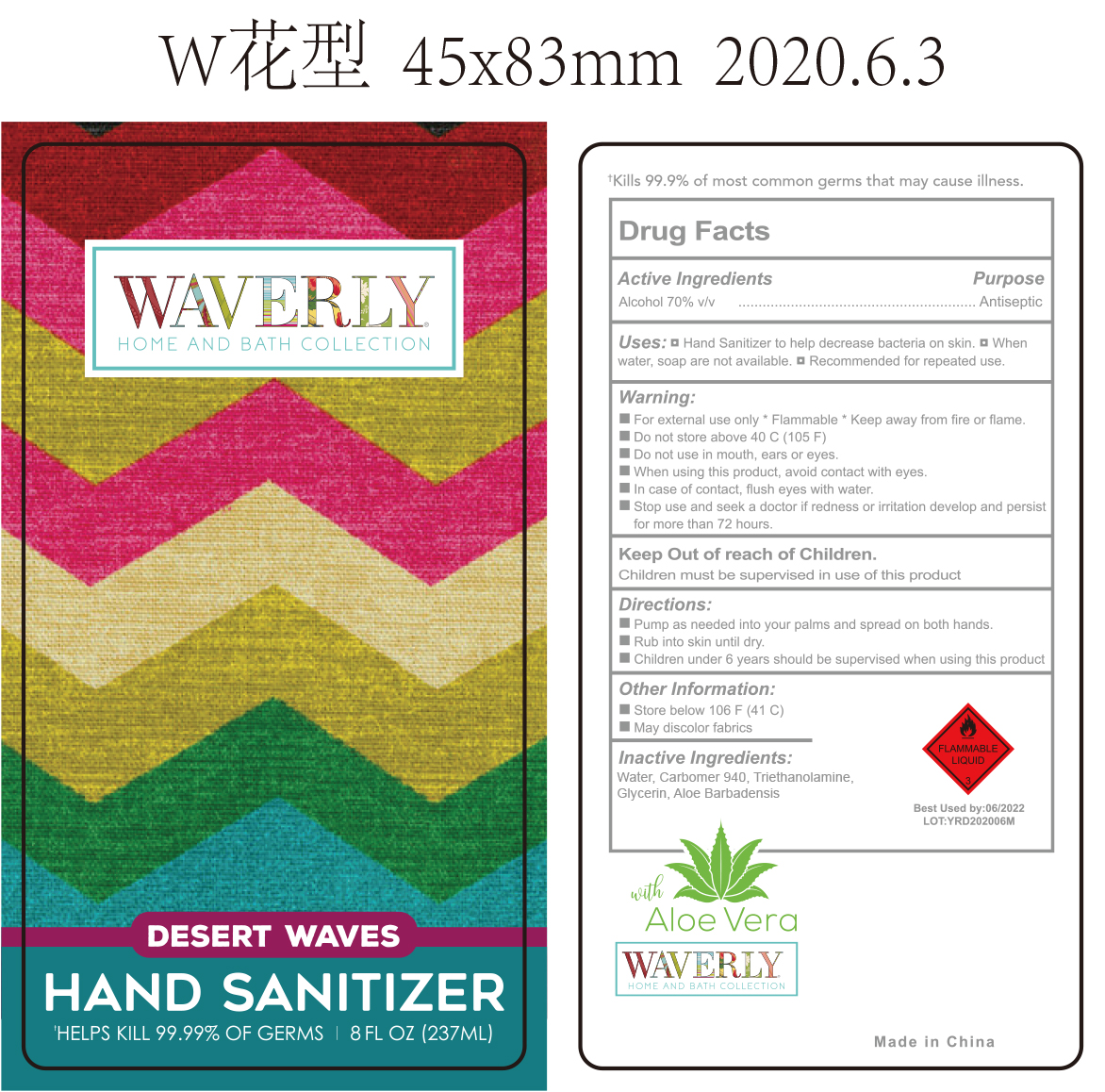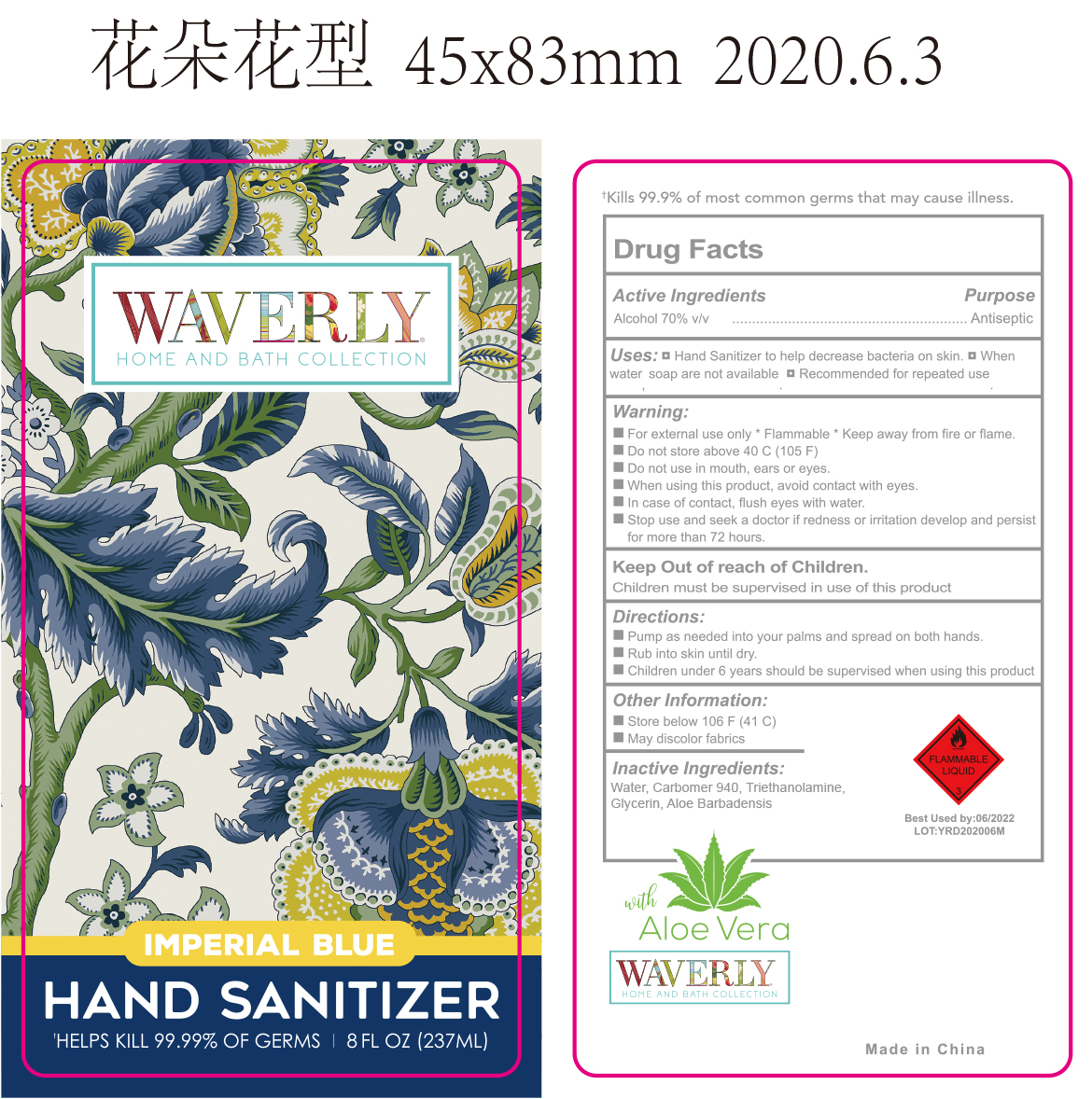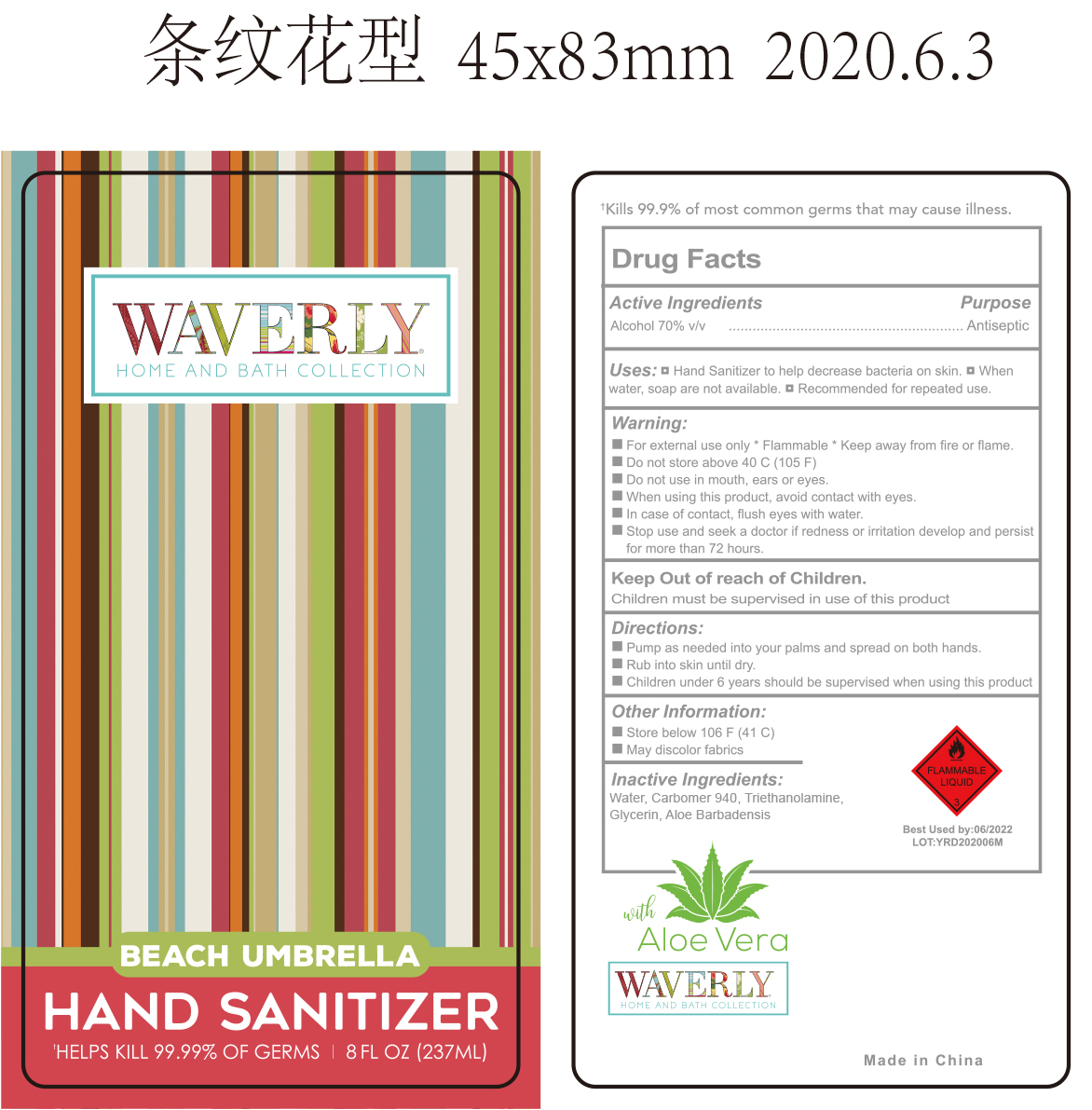 DRUG LABEL: HAND SANITIZER
NDC: 47993-295 | Form: GEL
Manufacturer: NINGBO JIANGBEI OCEAN STAR TRADING CO.,LTD
Category: otc | Type: HUMAN OTC DRUG LABEL
Date: 20201105

ACTIVE INGREDIENTS: ALCOHOL 70 mL/100 mL
INACTIVE INGREDIENTS: WATER; CARBOMER 940; TRIETHANOLAMINE BENZOATE; GLYCERIN; ALOE VERA LEAF

47993-295

Active ingredients

Alcohol 70% V/V

PURPOSE

Antiseptic

Uses：

- Hand sanitizer to help decrease bacteria on skin.
- When water, soap are not available.
- Recommended for repeated use.

Warnings:

- For external use only*Flammable*Keep away from fire or flame.
- Do not store above 40℃ (105℉).

- Do not use in mouth, ears or eyes.

- When using this product, avoid contact with eyes.
- In case of contact, flush eyes with water.

- Stop use and seek a doctor if redness or irritation develop and persist for more than 72 hours.

Keep out of reach of children.

Children must be supervised in use of this product.

Directions:

- Pump as needed into your palms and spread on both hands.
- Rub into skin until dry.
- Children under 6 years should be supervisd when using this product.

Other information：

- Store below 106℉(41℃)
- May discolor fabrics

Inactive Ingredients:

Water,Carbomer940,Triethanolamine,Glycerin,Aloe Barbadensis.